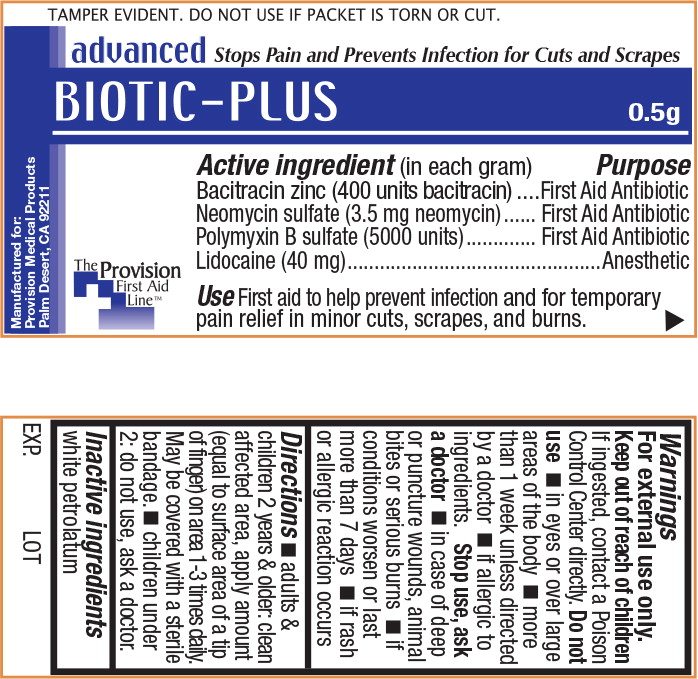 DRUG LABEL: Biotic-Plus
NDC: 69103-2400 | Form: OINTMENT
Manufacturer: Provision Medical
Category: otc | Type: HUMAN OTC DRUG LABEL
Date: 20140724

ACTIVE INGREDIENTS: bacitracin zinc 400 [iU]/1 g; neomycin sulfate 3.5 mg/1 g; polymyxin b sulfate 5000 [iU]/1 g; lidocaine .40 mg/1 g
INACTIVE INGREDIENTS: petrolatum

TAMPER EVIDENT. DO NOT USE IF PACKET IS TORN OR CUT.

advanced Stops Pain and Prevents Infection for Cuts and Scrapes

BIOTIC-PLUS 0.5g

Active ingredients

(in each gram)

Bacitracin zinc (400 units Bacitracin)

Neomycin sulfate (3.5 mg neomycin)

Polymyxin B sulfate (5000 units)

Lidocaine .40 mg

Purpose

First Aid Antibiotic

First Aid Antibiotic

First Aid Antibiotic

Anesthetic

Uses

First aid to help prevent infection and provide temporary relief in minor cuts, scrapes, and burns

The Provision First Aid Line

Manufactured for Provision Medical Products Palm Desert, CA 92211

Warnings

For external use only.

Keep out of reach of children

If ingested, contact a Poison Control Center directly.

Do not use

- in eyes or over large areas of the body
- more than 1 week unless directed by a doctor
- if allergic to ingredients.

Stop use, ask a doctor

- in case of deep or puncture wounds, animal bites or serious burns
- if conditions worsen or last more than 7 days
- if rash or allergic reaction occurs

Directions

- adults & children 2 years & older: clean affected area, apply amount (equal to surface area of a tip of finger) on area 1-3 times daily. May be covered with a sterile bandage.
- children under 2: do not use, ask a doctor

Inactive ingredients

white petrolatum